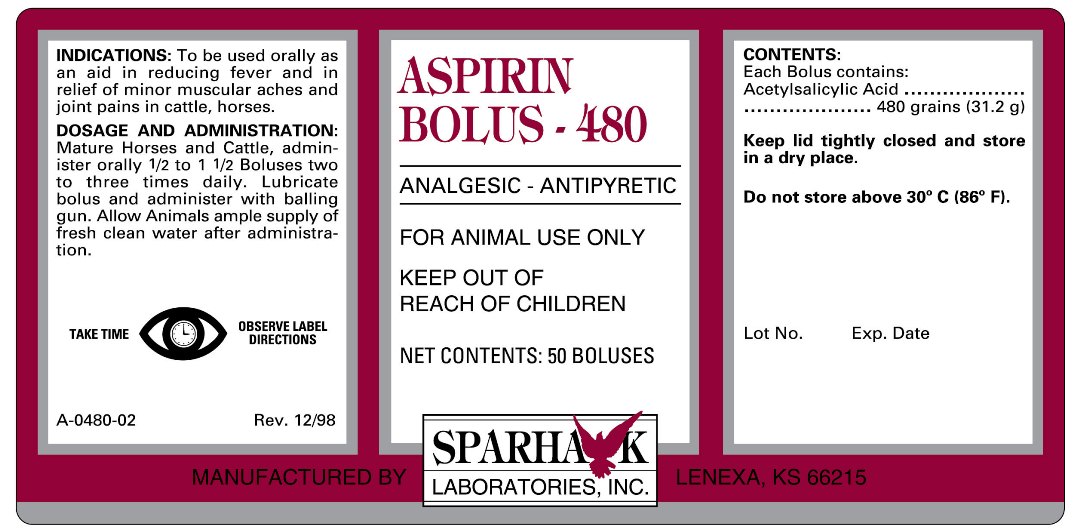 DRUG LABEL: ASPIRIN BOLUS - 480
NDC: 58005-480 | Form: TABLET
Manufacturer: Sparhawk Laboratories, Inc.
Category: animal | Type: OTC ANIMAL DRUG LABEL
Date: 20120605

ACTIVE INGREDIENTS: ASPIRIN 31.2 g/1 1

ASPIRIN BOLUS - 480 ANALGESIC - ANTIPYRETIC

INDICATIONS

To be used orally as an aid in reducing fever and in relief of minor muscular aches and joint pains in cattle, horses.

DOSAGE AND ADMINISTRATION

Mature Horses and Cattle, administer orally 1/2 to 1 1/2 Boluses two to three times daily. Lubricate bolus and administer with balling gun. Allow Animals ample supply of fresh clean water after administration.

TAKE TIME OBSERVE LABEL DIRECTIONS

CONTENTS

Each Bolus contains:

Acetylsalicylic Acid..........480 grains (31.2 g)

STORAGE AND HANDLING

Keep lid tightly closed and store in a dry place

Do not store above 30o C (86o F)

PACKAGE LABEL

FOR ANIMAL USE ONLY

KEEP OUT OF REACH OF CHILDREN